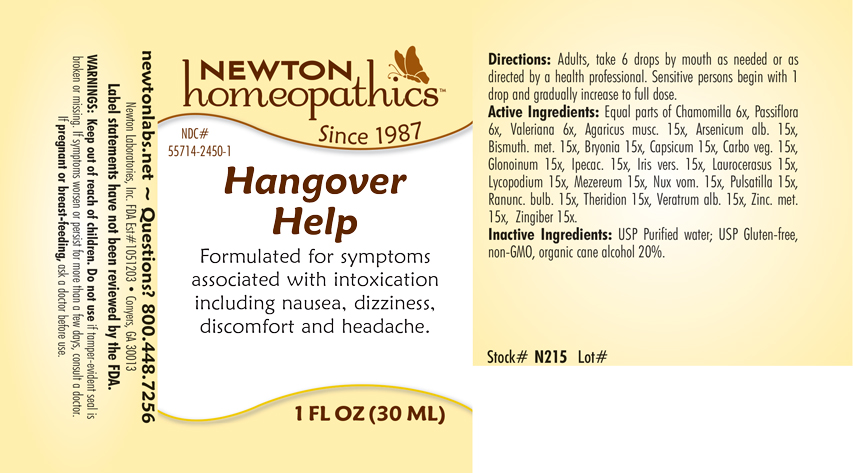 DRUG LABEL: Hangover Help
NDC: 55714-2450 | Form: LIQUID
Manufacturer: Newton Laboratories, Inc.
Category: homeopathic | Type: HUMAN OTC DRUG LABEL
Date: 20250206

ACTIVE INGREDIENTS: AMANITA MUSCARIA FRUITING BODY 15 [hp_X]/1 mL; ARSENIC TRIOXIDE 15 [hp_X]/1 mL; BISMUTH 15 [hp_X]/1 mL; BRYONIA ALBA ROOT 15 [hp_X]/1 mL; CAPSICUM 15 [hp_X]/1 mL; ACTIVATED CHARCOAL 15 [hp_X]/1 mL; NITROGLYCERIN 15 [hp_X]/1 mL; IPECAC 15 [hp_X]/1 mL; IRIS VERSICOLOR ROOT 15 [hp_X]/1 mL; PRUNUS LAUROCERASUS LEAF 15 [hp_X]/1 mL; LYCOPODIUM CLAVATUM SPORE 15 [hp_X]/1 mL; DAPHNE MEZEREUM BARK 15 [hp_X]/1 mL; STRYCHNOS NUX-VOMICA SEED 15 [hp_X]/1 mL; ANEMONE PULSATILLA 15 [hp_X]/1 mL; RANUNCULUS BULBOSUS 15 [hp_X]/1 mL; THERIDION CURASSAVICUM 15 [hp_X]/1 mL; VERATRUM ALBUM ROOT 15 [hp_X]/1 mL; ZINC 15 [hp_X]/1 mL; GINGER 15 [hp_X]/1 mL; MATRICARIA CHAMOMILLA 6 [hp_X]/1 mL; PASSIFLORA INCARNATA FLOWERING TOP 6 [hp_X]/1 mL; VALERIAN 6 [hp_X]/1 mL
INACTIVE INGREDIENTS: ALCOHOL; WATER

Hangover 2450L

INDICATIONS & USAGE SECTION

Formulated for symptoms associated with intoxication including nausea, dizziness, discomfort and headache.

DOSAGE & ADMINISTRATION SECTION

Directions: Adults, take 6 drops by mouth as needed or as directed by a healthcare professional. Sensitive persons begin with 1 drop and gradually increase to full dose.

OTC - ACTIVE INGREDIENT SECTION

Equal parts of Chamomilla 6x, Passiflora 6x, Valeriana 6x, Agaricus musc. 15x, Arsenicum alb. 15x, Bismuthum metallicum 15x, Bryonia 15x, Capsicum 15x, Carbo veg.15x, Glonoinum 15x, Ipecac. 15x, Iris versicolor 15x, Laurocerasus 15x, Lycopodium 15x, Mezereum 15x, Nux vom. 15x, Pulsatilla 15x, Ranunc. bulb. 15x, Theridion 15x, Veratrum alb. 15x, Zinc. met. 15x, Zingiber 15x.

OTC - PURPOSE SECTION

Formulated for symptoms associated with intoxication including nausea, dizziness, discomfort and headache.

INACTIVE INGREDIENT SECTION

Inactive Ingredients: USP Purified Water; USP Gluten-free, non-GMO, organic cane alcohol 20%.

QUESTIONS SECTION

newtonlabs.net – Questions? 800.448.7256

Newton Laboratories, Inc. FDA Est # 1051203 - Conyers, GA 30013

WARNINGS SECTION

WARNINGS: Keep out of reach of children. Do not use if tamper-evident seal is broken or missing. If symptoms worsen or persist for more than a few days, consult a doctor. If pregnant or breast-feeding, ask a doctor before use.

OTC - PREGNANCY OR BREAST FEEDING SECTION

If pregnant or breast-feeding, ask a doctor before use.

OTC - KEEP OUT OF REACH OF CHILDREN SECTION

Keep out of reach of children.